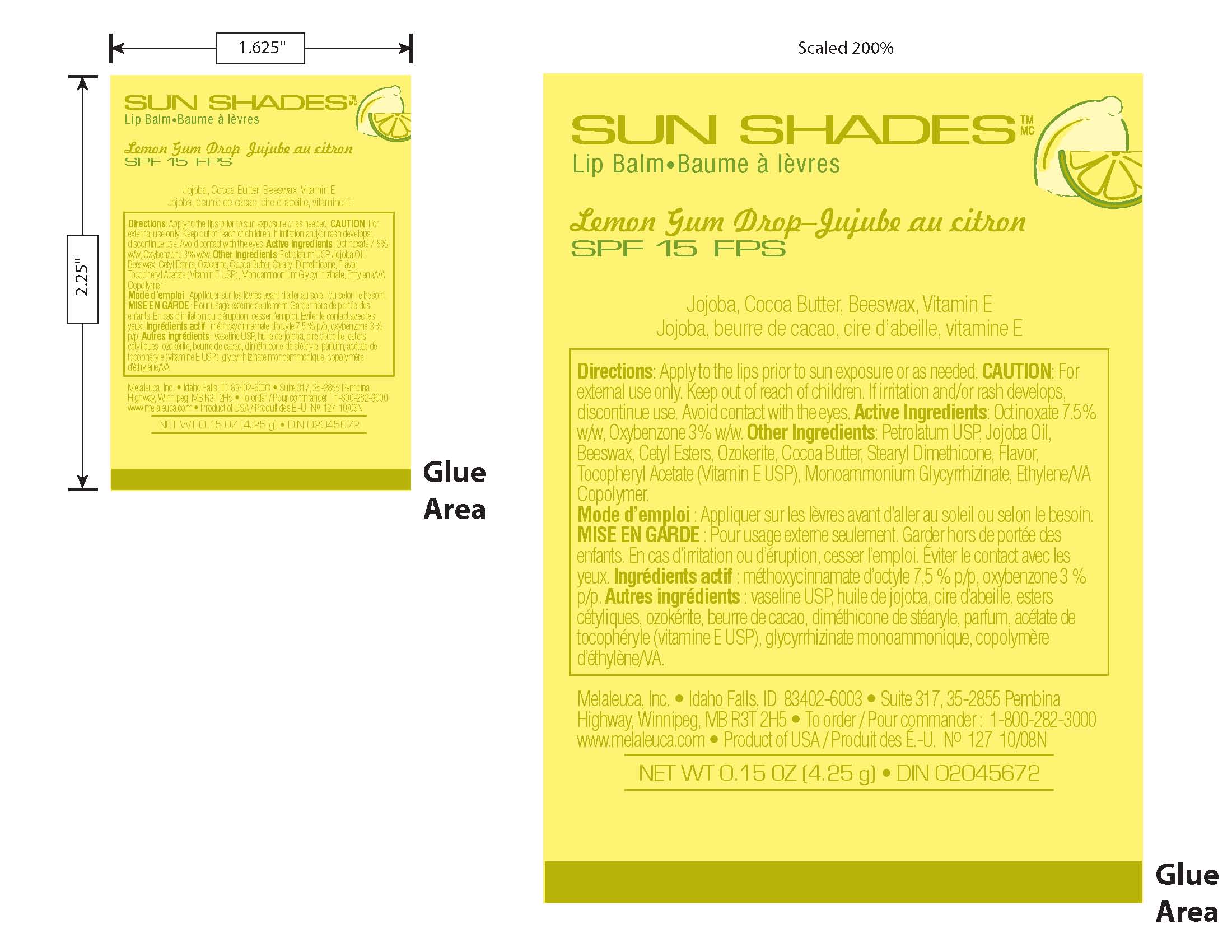 DRUG LABEL: SUN SHADES
NDC: 54473-162 | Form: STICK
Manufacturer: Melaleuca, Inc.
Category: otc | Type: HUMAN OTC DRUG LABEL
Date: 20101230

ACTIVE INGREDIENTS: Octinoxate 75 mg/1 g; Oxybenzone 30 mg/1 g
INACTIVE INGREDIENTS: Jojoba Oil; Yellow Wax; Cetyl Esters Wax; Ceresin; Cocoa Butter; Vitamin E Acetate; ETHYLENE-VINYL ACETATE COPOLYMER (40% VINYL ACETATE); Glycyrrhizin, Ammoniated; Petrolatum

SUN SHADES Lemon Gum Drop Label Information

DOSAGE AND ADMINISTRATION

Directions: Apply to the lips prior to sun exposure or as needed.

WARNINGS

Caution: For external use only. Keep out of reach of children. If irritation develops, discontinue use. Avoid contact with the eyes.

ACTIVE INGREDIENT

Active Ingredients: Octinoxate 7.5% w/w. Oxybenzone 3.0% w/w.

INACTIVE INGREDIENT

Other Ingredients: Petrolatum USP, Jojoba Oil, Beeswax, Cetyl Esters, Ozokerite, Cocoa Butter, Stearyl Dimethicone, Flavor, Tocopheryl Acetate (Vitamin E USP), Monoammonium Glycyrrhizinate, Ethylene VA Copolymer.